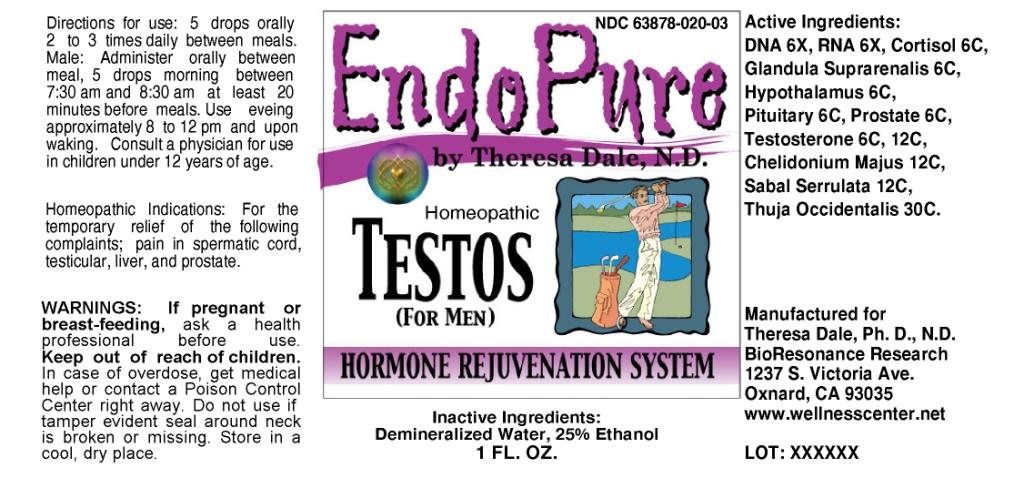 DRUG LABEL: Endopure Testos-Male
NDC: 57520-0143 | Form: LIQUID
Manufacturer: Apotheca Company
Category: homeopathic | Type: HUMAN OTC DRUG LABEL
Date: 20100803

ACTIVE INGREDIENTS: HERRING SPERM DNA 6 [hp_X]/1 mL; SACCHAROMYCES CEREVISIAE RNA 6 [hp_X]/1 mL; HYDROCORTISONE 6 [hp_C]/1 mL; SUS SCROFA HYPOTHALAMUS 6 [hp_C]/1 mL; SUS SCROFA PITUITARY GLAND 6 [hp_C]/1 mL; SUS SCROFA PROSTATE 6 [hp_C]/1 mL; TESTOSTERONE 12 [hp_C]/1 mL; CHELIDONIUM MAJUS 12 [hp_C]/1 mL; SAW PALMETTO 12 [hp_C]/1 mL; THUJA OCCIDENTALIS LEAFY TWIG 30 [hp_C]/1 mL; SUS SCROFA ADRENAL GLAND 6 [hp_C]/1 mL
INACTIVE INGREDIENTS: WATER; ALCOHOL

Endopure Testos-Male

ACTIVE INGREDIENT

ACTIVE INGREDIENTS: DNA 6X, RNA 6X, Cortisol 6C, Glandula Suprarenalis 6C, Hypothalamus 6C, Pituitary 6C, Prostate 6C, Testosterone 6C, 12C, Chelidonium Majus 12C, Sabal Serrulata 12C, Thuja Occidentalis 30C.

PURPOSE

HOMEOPATHIC INDICATIONS: For the temporary relief of the following complaints; pain in spermatic cord, testicular, liver, and prostate.

WARNINGS

WARNINGS: If pregnant of breast-feeding, ask a health professional before use. Keep out of reach of children. In case of overdose, get medical help or contact a Poison Control Center right away. Do not use if tamper evident seal around neck is broken or missing. Store in a cool, dry place.

DOSAGE AND ADMINISTRATION

DIRECTIONS FOR USE: 5 drops orally 2 to 3 times daily between meals. Male: Administer orally between meal, 5 drops morning between 7:30 am and 8:30 am at least 20 minutes before meals. Use evening approximately 8 to 12 pm and upon waking. Consult a physician for use in children under 12 years of age.

INACTIVE INGREDIENTS: Demineralized Water, 25% Ethanol

QUESTIONS

Manufactured for: Theresa Dale, Ph. D., N.D.

BioResonance Research

1237 S. Victoria Ave.

Oxnard, CA 93035

www.wellnesscenter.net

PACKAGE LABEL

ENDOPURE TESTOS (FOR MEN)

Homeopathic

1 FL. OZ.